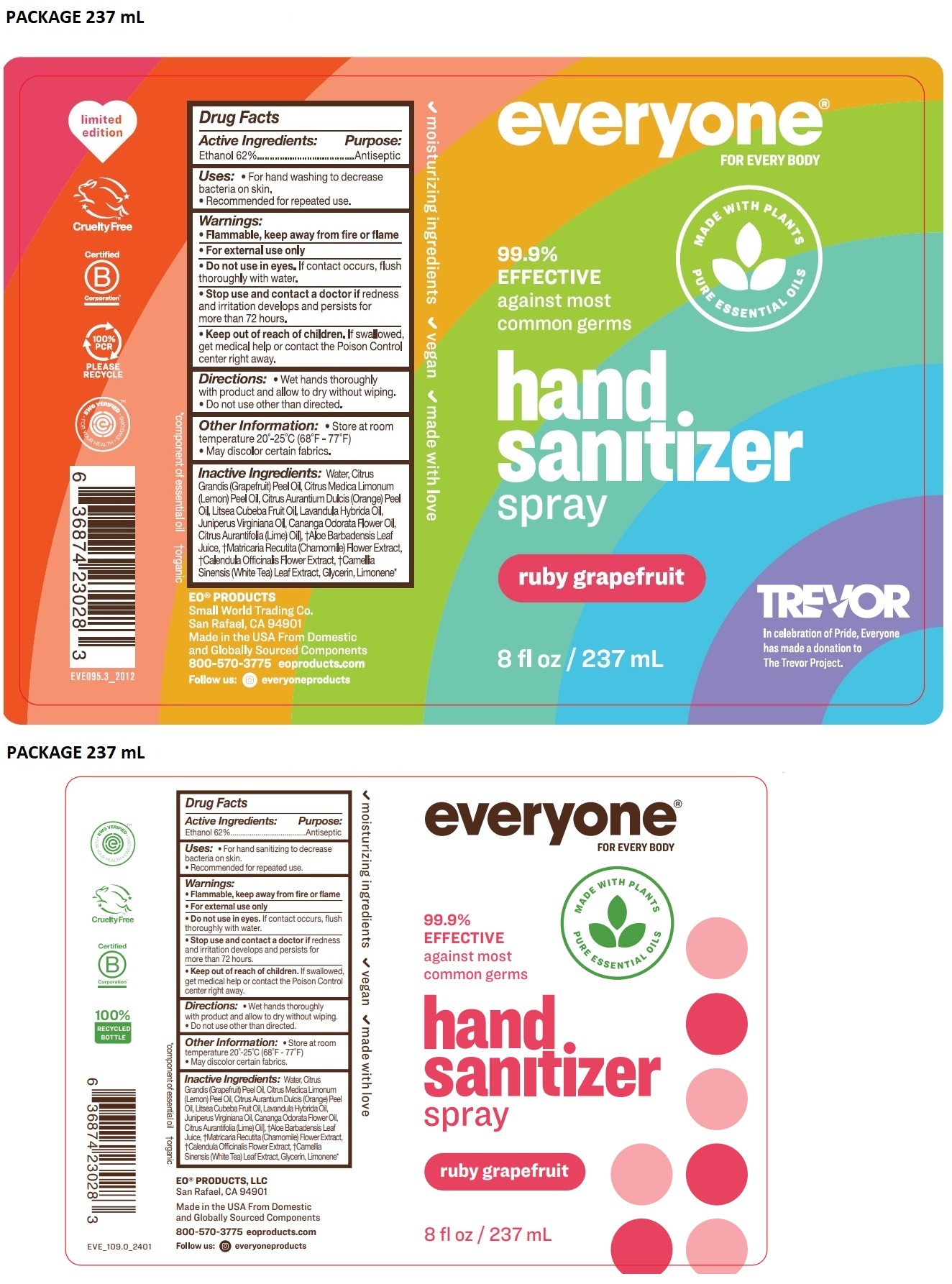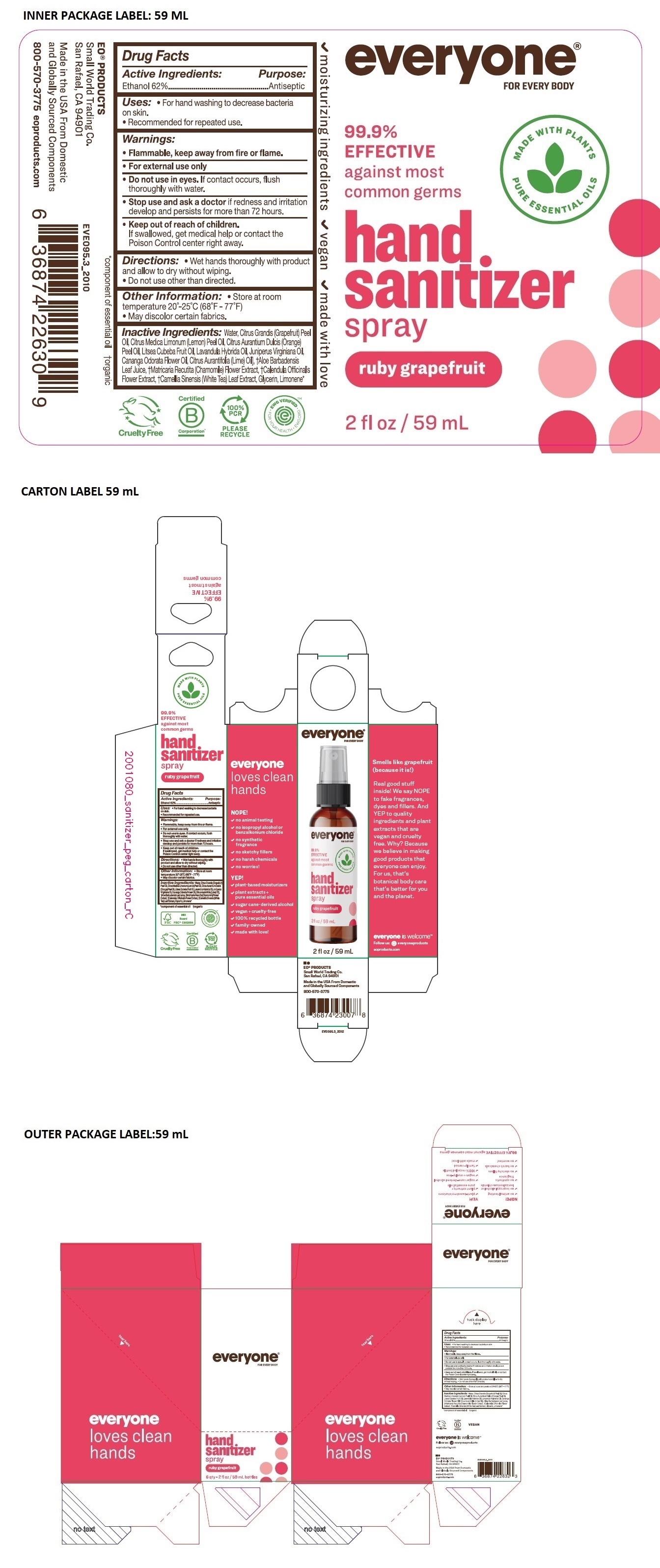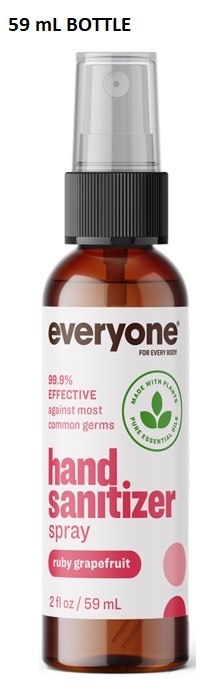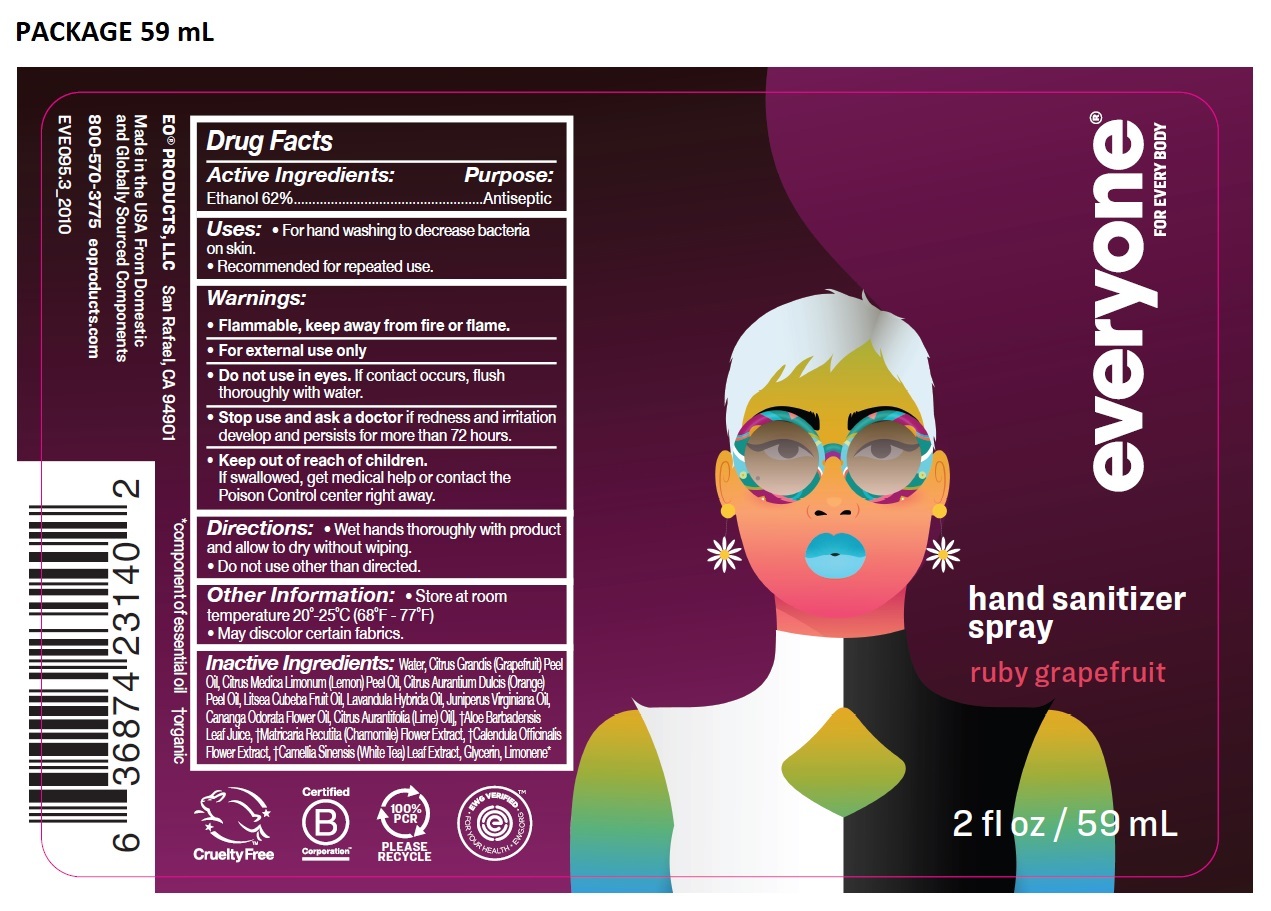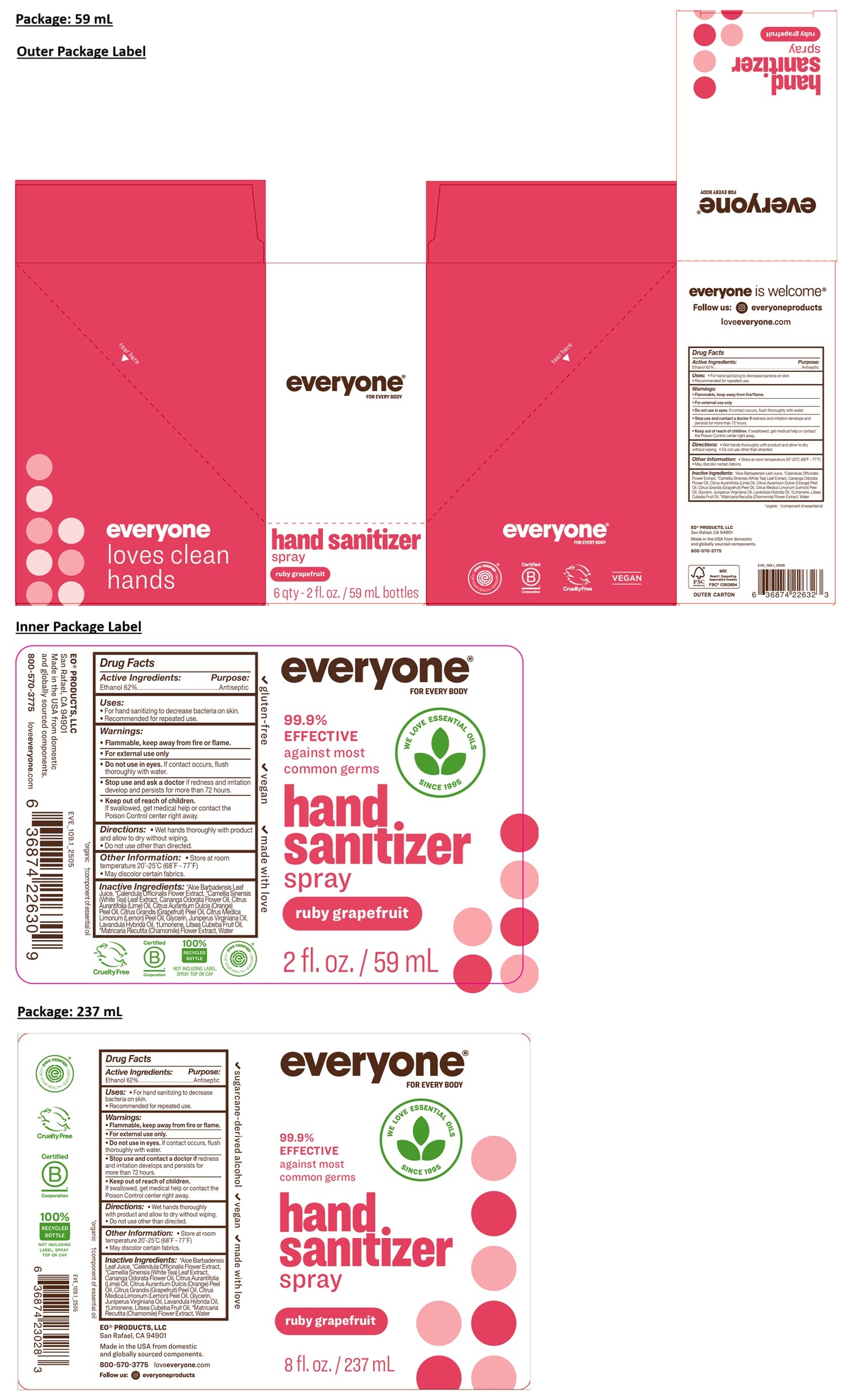 DRUG LABEL: everyone hand sanitizer
NDC: 54748-604 | Form: SPRAY
Manufacturer: EO Products, LLC
Category: otc | Type: HUMAN OTC DRUG LABEL
Date: 20251124

ACTIVE INGREDIENTS: ALCOHOL 62 mL/100 mL
INACTIVE INGREDIENTS: ALOE VERA LEAF JUICE; CALENDULA OFFICINALIS FLOWER; WHITE TEA; YLANG-YLANG OIL; LIME OIL, COLD PRESSED; ORANGE OIL, COLD PRESSED; CITRUS MAXIMA FRUIT RIND OIL; LEMON OIL, COLD PRESSED; GLYCERIN; JUNIPERUS VIRGINIANA OIL; LAVANDIN OIL; LIMONENE, (+)-; LITSEA OIL; CHAMOMILE; WATER

everyone® FOR EVERY BODY hand sanitizer spray ruby grapefruit

Active Ingredients:

Ethanol 62%

Purpose:

Antiseptic

Uses:

• For hand sanitizing to decrease bacteria on skin.

• Recommended for repeated use.

Warnings:

• Flammable, keep away from fire/flame.

• For external use only

• Do not use in eyes. If contact occurs, flush thoroughly with water.

• Stop use and contact a doctor if redness and irritation develops and persists for more than 72 hours.

• Keep out of reach of children. If swallowed, get medical help or contact the Poison Control center right away.

Directions:

• Wet hands thoroughly with product and allow to dry without wiping. • Do not use other than directed.

Other Information:

• Store at room temperature 20°-25°C (68°F - 77°F)

• May discolor certain fabrics.

Inactive Ingredients:

*Aloe Barbadensis Leaf Juice, *Calendula Officinalis Flower Extract, *Camellia Sinensis (White Tea) Leaf Extract, Cananga Odorata Flower Oil, Citrus Aurantifolia (Lime) Oil, Citrus Aurantium Dulcis (Orange) Peel Oil, Citrus Grandis (Grapefruit) Peel Oil, Citrus Medica Limonum (Lemon) Peel Oil, Glycerin, Juniperus Virginiana Oil, Lavandula Hybrida Oil, †Limonene, Litsea Cubeba Fruit Oil, *Matricaria Recutita (Chamomile) Flower Extract, Water

*organic †component of essential oil

Cruelty Free

VEGAN

everyone is welcome®

Follow us: everyoneproducts

loveeveryone.com

EO® PRODUCTS, LLC
San Rafael, CA 94901

Made in the USA from domestic and globally sourced components.

800-570-3775

everyone loves clean hands

WE LOVE ESSENTIAL OILS SINCE 1995

99.9% EFFECTIVE against most common germs

✓ gluten-free

✓ sugarcane-derived alcohol

✓ made with love